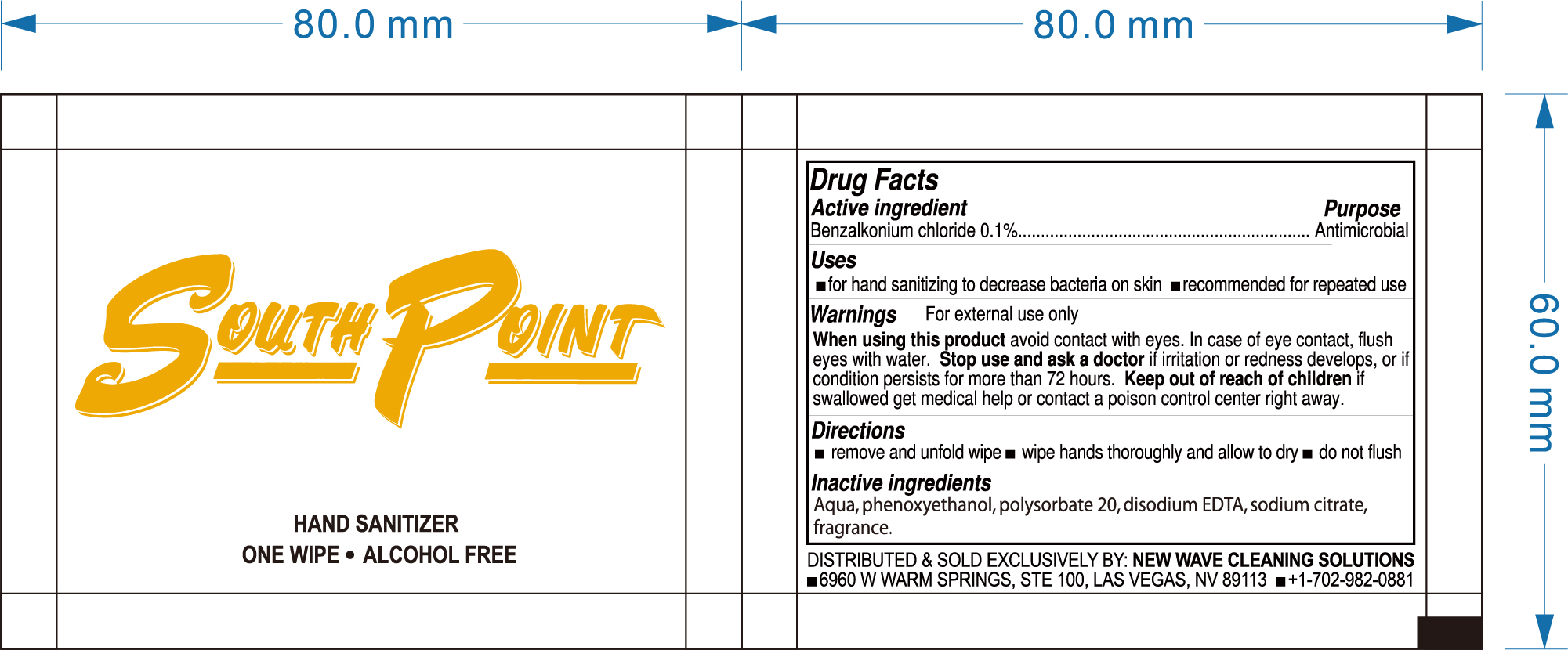 DRUG LABEL: SouthPoint sanitizer wipe
NDC: 54860-327 | Form: CLOTH
Manufacturer: Shenzhen Lantern Science Co.,Ltd.
Category: otc | Type: HUMAN OTC DRUG LABEL
Date: 20200830

ACTIVE INGREDIENTS: BENZALKONIUM CHLORIDE 0.1 1/100 1
INACTIVE INGREDIENTS: PEACH 0.05 1/100 1; SODIUM CITRATE 0.05 1/100 1; WATER 99.1 1/100 1; POLYSORBATE 20 0.15 1/100 1; EDETATE DISODIUM ANHYDROUS 0.1 1/100 1; PHENOXYETHANOL 0.45 1/100 1

SouthPoint sanitizer wipe

Active ingredient

Active ingredient purpose

Benzalkonium Chloride 0.1% Antimicrobial

Use

for hand sanitizing to decrease bacteria on skin

recommended for repeated use.

warnings

For external use only.

When using this product

Avoid contact with eyes.In case of eye contact,flush eyes with water.

Stop use and ask a doctor

if irritation or redness develops,or if condition persists for more than 72 hours.

Keep out of reach of children

if swallowed,get medical help or contact a Poison Control Center right away.

Directions

remove and unfold wipe

wipe hands thoroughly and allow to dry

do not flush

Inactive ingredient

Aqua,phenoxyethanol,polysorbate 20,disodium EDTA,sodium citrate,fragrance.

usage

Remove and unfold wipe

wipe hands thoroughly and allow to dry.

do not flush